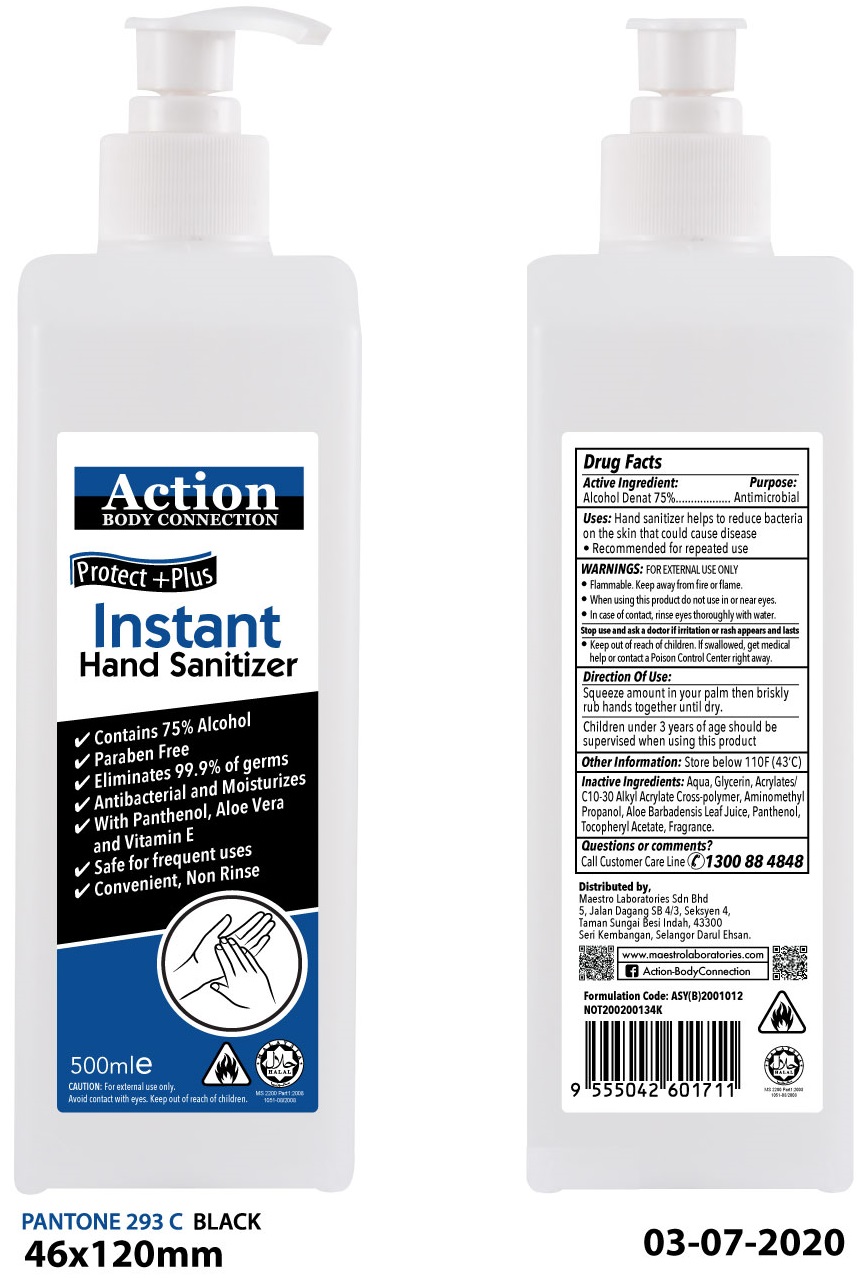 DRUG LABEL: Action Instant Hand Sanitizer
NDC: 80613-000 | Form: GEL
Manufacturer: MAESTRO LABORATORIES SDN. BHD.
Category: otc | Type: HUMAN OTC DRUG LABEL
Date: 20200918

ACTIVE INGREDIENTS: ALCOHOL 0.75 mL/1 mL
INACTIVE INGREDIENTS: WATER; GLYCERIN; CARBOMER INTERPOLYMER TYPE A (ALLYL SUCROSE CROSSLINKED); AMINOMETHYLPROPANOL; ALOE VERA LEAF; PANTHENOL; .ALPHA.-TOCOPHEROL ACETATE

Action Instant Hand Sanitizer

Active Ingredient:

Alcohol Denat 75%

Purpose

Antimicrobial

Uses:

- Hand sanitizer helps to reduce bacteria on the skin that could cause disease
- Recommended for repeated use

WARNINGS:

FOR EXTERNAL USE ONLY

- Flammable. Keep away from fire or flame.

When using this product

- do not use in or near eyes.
- In case of contact, rinse eyes thoroughly with water.

Stop use and ask a doctor

if irritation or rash appears and lasts

Keep out of reach of children.

- If swallowed, get medical help or contact a Poison Control Center right away.

Direction Of Use:

Squeeze amount in your palm then briskly rub hands together until dry.

Children under 3 years of age should be supervised when using this product

Other Information:

Store below 110F (43C)

Inactive Ingredients:

Aqua, Glycerin, Acrylates/C10-30 Alkyl Acrylate Cross-polymer, Aminomethyl Propanol, Aloe Barbadensis Leaf Juice, Panthenol, Tocopheryl Acetate, Fragrance.

Questions or comments?

Call Customer Care Line 1300 88 4848